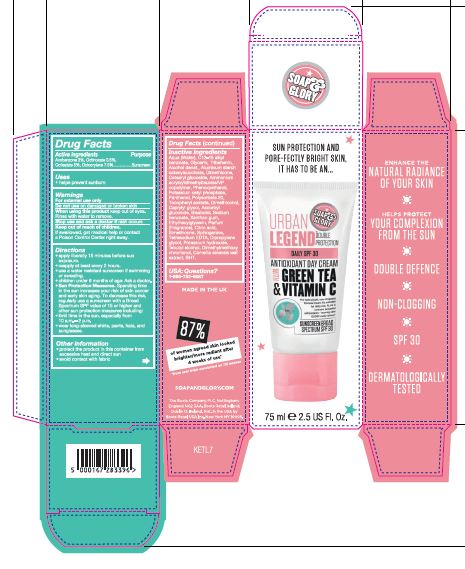 DRUG LABEL: Urban Legend Antioxidant Day Cream with Green Tea and Vitamin C Sunscreen Broad Spectrum SPF 30
NDC: 11489-154 | Form: CREAM
Manufacturer: BCM Ltd
Category: otc | Type: HUMAN OTC DRUG LABEL
Date: 20191007

ACTIVE INGREDIENTS: AVOBENZONE 2.25 g/75 g; OCTINOXATE 0.375 g/75 g; OCTISALATE 3.75 g/75 g; OCTOCRYLENE 5.625 g/75 g
INACTIVE INGREDIENTS: WATER; ALKYL (C12-15) BENZOATE; GLYCERIN; TRIBEHENIN; ALCOHOL; DIMETHICONE; ALUMINUM STARCH OCTENYLSUCCINATE; CETEARYL GLUCOSIDE; AMMONIUM ACRYLOYLDIMETHYLTAURATE/VP COPOLYMER; POTASSIUM CETYL PHOSPHATE; PHENOXYETHANOL; PANTHENOL; .ALPHA.-TOCOPHEROL ACETATE; POLYSORBATE 20; DIMETHICONOL (2000 CST); CAPRYLYL GLYCOL; ASCORBYL GLUCOSIDE; XANTHAN GUM; SODIUM BENZOATE; .ALPHA.-BISABOLOL, (+)-; ETHYLHEXYLGLYCERIN; CITRIC ACID MONOHYDRATE; SPHINGANINE; EDETATE SODIUM TETRAHYDRATE; DIPROPYLENE GLYCOL; POTASSIUM HYDROXIDE; TERT-BUTYL ALCOHOL; DIMETHYLMETHOXY CHROMANOL; SILICA DIMETHYL SILYLATE; GREEN TEA LEAF; BUTYLATED HYDROXYTOLUENE

Soap and Glory Urban Legend Antioxidant Day Cream with Green Tea and Vitamin C Sunscreen Broad Spectrum SPF 30

Carton

Active ingredients

Avobenzone 3%

Octinoxate 0.5%

Octisalate 5%

Octocrylene 7.5%

Purpose

Sunscreen

Uses

- Uses helps prevent sunburn

Warnings

For external use only

Do not use on damaged or broken skin

When using this product keep out of eyes. Rinse with water to remove.

Ask Doctor section

Stop use and ask a doctor if rash occurs

Keep out of reach of children.

If swallowed, get medical help or contact a Poison Control Centre right away

Directions

- Apply liberally 15 minutes before sun exposure
- reapply at least every 2 hours
- use a water resistant sunscreen if swimming or sweating
- children under 6 months of age: Ask a doctor
- Sun Protection Measures. Spending time in the sun increases your risk of skin cancer and early skin aging. To decrease this risk, regularly use a sunscreen with a Broad Spectrum SPF value of 15 or higher and other sun protection measures including:
- Limit time in the sun, especially from 10 a.m - 2 p.m.
- wear long-sleeved shirts,pants,hats and sunglasses.

Other information

- protect the product in this container from excessive heat and direct sun
- avoid contact with fabric

Inactive ingredients

Inactive ingredients Aqua (Water), C12-15 alkyl benzoate, Glycerin, Tribehenin, Alcohol denat., Aluminum starch octenylsuccinate, Dimethicone, Cetearyl glucoside, Ammonium acryloldimethyltaurate/VP copolymer, Phenoxyethanol, Potassium cetyl phosphate, Panthenol, Tocopheryl acetate, Polysorbate 20, Dimethiconol, Caprylyl glycol, Ascorbyl glucoside, Sodium benzoate, Bisabolol, Xanthan gum, Ethylhexylglycerin, Parfum (Fragrance), Citric acid, Simethicone, Sphinganine, Tetrasodium EDTA, Dipropylene glycol, Potassium hydroxide, T-butyl alcohol, Dimethylmethoxy chromanol, Camellia sinensis leaf extract, BHT.

Questions

USA: Questions? 1-866-752-6687

Information

Manufactured for The Boots Company PLC Nottingham England NG2 3AA. Boots Retail Ireland Dublin 12 Ireland.

Dist. in the USA by Boots Retail USA, New York, NY 10005

Made in the UK

soapandglory.com

Description

Sun Protection and pore-fectly bright skin. It has to be an...

This lightweight, non-clogging formula means it's suitable for daily use. Plus, it contains powerful antioxidants, leaving skin GLORY-ously glowy!

Enhance the natural radiance of your skin.

Helps protect your complexion from the sun.

Double Defence

Non-clogging

Sunscreen Broad Spectrum SPF 30

Dermatologically tested.

87% of women agreed their skin looked brighter/more radiant after 4 weeks of use.*

*from user trials conducted on 115 women

Manufactured for The Boots Company PLC Nottingham England NG2 3AA. Boots Retail Ireland Dublin 12 Ireland.

Dist. in the USA by Boots Retail USA, New York, NY 10005

Made in the UK

soapandglory.com

Tube wording

Soap & Glory Urban Legend Antioxidant Day Cream with Green Tea and Vitamin C Sunscreen Broad Spectrum SPF 30

This lightweight, non-clogging formula means it's suitable for daily use. Plus, it contains powerful antioxidants, leaving skin GLORY-ously glowy!

Enhance the natural radiance of your skin, wh ile helping protect to your complexion from the sun with our double-defence, non-clogging, protecting day cream.

Every day, apply liberally cheeks, chin & forehead. Using our fingertips, gently blend into the skin making sure every last little bit is covered.

Warning: Avoid contact with the eyes. If contact with eyes occurs, rinse thoroughly with warm water. This product is not designed for sunbathing. Avoid contact with fabric.

Active Ingredients: Avobenzone 3% Octinoxate 0.5% Octisalate 5% Octocrylene 7.5%

Manufactured for The Boots Company PLC Nottingham England NG2 3AA. Boots Retail Ireland Dublin 12 Ireland.

Dist. in the USA by Boots Retail USA, New York, NY 10005

Made in the UK

soapandglory.com

Carton